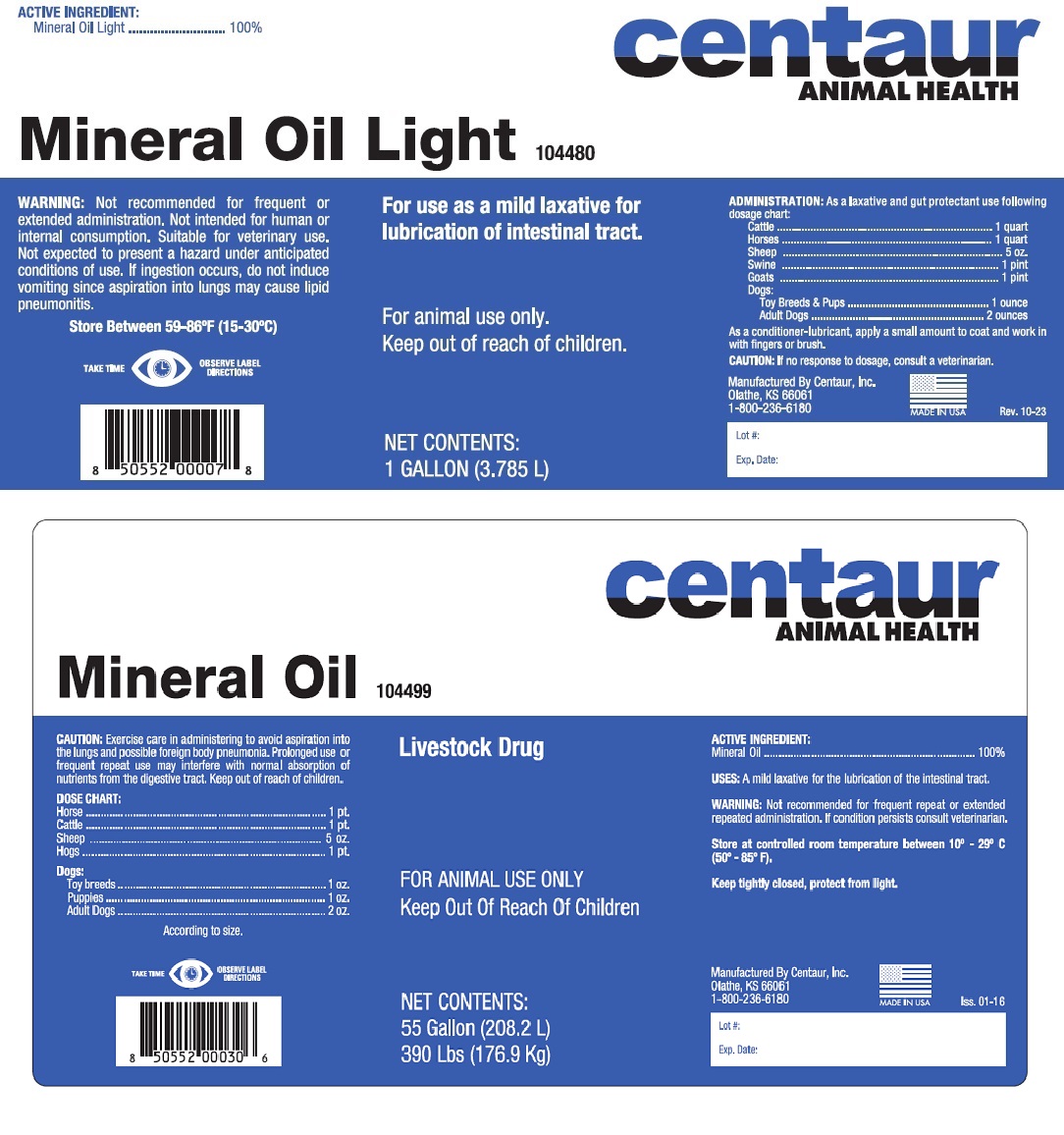 DRUG LABEL: Mineral Oil
NDC: 58305-044 | Form: OIL
Manufacturer: Centaur, Inc.
Category: animal | Type: OTC ANIMAL DRUG LABEL
Date: 20251126

ACTIVE INGREDIENTS: Light Mineral Oil 3.785 L/3.785 L

WARNINGS AND PRECAUTIONS

Mineral Oil Light

For use as a mild laxative for lubrication of intestinal tract.

For animal use only

Keep out of reach of children

ACTIVE INGREDIENTS:

Mineral Oil Light ................. 100%

WARNING: Not recommended for frequent or extended administration. Not intended for human or internal consumption. Suitable for veterinary use. Not expected to present a hazard under anticipated conditions of use. If ingestion occurs, do not induce vomiting since aspiration into lungs may cause lipid pneumonitis.

Store Between 59-86°F (15-30°C)

ADMINISTRATION: As a laxative and gut protectant use following dosage chart:

Cattle........................................1 quart

Horses......................................1 quart

Sheep.......................................5 oz

Swine.......................................1 pint

Goats.......................................1 pint

Dogs:

Toy Breeds and Pups.............1 ounce

Adult Dogs.............................2 ounces

As a conditioner-lubricant, apply a small amount to coat and work in with fingers or brush.

CAUTION: If no response to dosage, consult a veterinarian.

Mineral Oil

Livestock Drug

For animal use only

Keep out of reach of children

ACTIVE INGREDIENTS:

Mineral Oil................. 100%

USES: A mild laxative for the lubrication of the intestinal tract.

WARNING: Not recommended for frequent repeat or extended repeated administration. If condition persists consult veterinarian.

Store at controlled room temperature between 10°-29°C (50°-85°F).

Keep tightly closed, protect from light.

CAUTION: Exercise care in administering to avoid aspiration into the lungs and possible foreign body pneumonia. Prolonged use or frequent repeat use may interfere with normal absorption of nutrient from the digestive tract. Keep out of reach of children.

DOSE CHART:

Horse......................................1 pt.

Cattle.......................................1 pt.

Sheep.......................................5 oz.

Hogs.........................................1 pt.

Swine.......................................1 pint

Goats.......................................1 pint

Dogs:

Toy breeds............................1 oz.

Puppies.................................1 oz.

Adult Dogs.............................2 oz.

According to size.